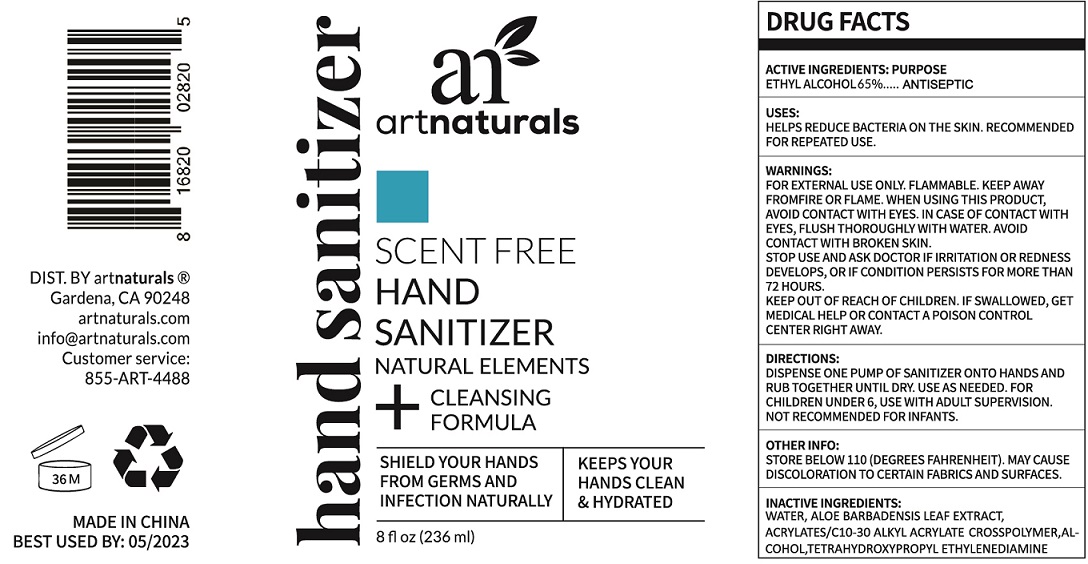 DRUG LABEL: HAND SANITIZER
NDC: 74642-002 | Form: GEL
Manufacturer: VIRGIN SCENT INC.
Category: otc | Type: HUMAN OTC DRUG LABEL
Date: 20200413

ACTIVE INGREDIENTS: ALCOHOL 0.65 mL/1 mL
INACTIVE INGREDIENTS: WATER; ALOE VERA LEAF; CARBOMER INTERPOLYMER TYPE A (ALLYL SUCROSE CROSSLINKED); EDETOL

HAND SANITIZER

ACTIVE INGREDIENTS:

ETHYL ALCOHOL 65%

PURPOSE

ANTISEPTIC

USES:

HELPS REDUCE BACTERIA ON THE SKIN. RECOMMENDED FOR REPEATED USE.

WARNINGS:

FOR EXTERNAL USE ONLY. FLAMMABLE. KEEP AWAY FROMFIRE OR FLAME.

WHEN USING THIS PRODUCT,

AVOID CONTACT WITH EYES. IN CASE OF CONTACT WITH EYES, FLUSH THOROUGHLY WITH WATER. AVOID CONTACT WITH BROKEN SKIN.

STOP USE AND ASK DOCTOR

IF IRRITATION OR REDNESS DEVELOPS, OR IF CONDITION PERSISTS FOR MORE THAN 72 HOURS.

KEEP OUT OF REACH OF CHILDREN.

IF SWALLOWED, GET MEDICAL HELP OR CONTACT A POISON CONTROL CENTER RIGHT AWAY.

DIRECTIONS:

DISPENSE ONE PUMP OF SANITIZER ONTO HANDS AND RUB TOGETHER UNTIL DRY. USE AS NEEDED. FOR CHILDREN UNDER 6, USE WITH ADULT SUPERVISION. NOT RECOMMENDED FOR INFANTS.

OTHER INFO:

STORE BELOW 110 (DEGREES FAHRENHEIT). MAY CAUSE DISCOLORATION TO CERTAIN FABRICS AND SURFACES.

INACTIVE INGREDIENTS

WATER, ALOE BARBADENSIS LEAF EXTRACT, ACRYLATES/C10-30 ALKYL ACRYLATE CROSSPOLYMER, ALCOHOL, TETRAHYDROXYPROPYL ETHYLENEDIAMINE